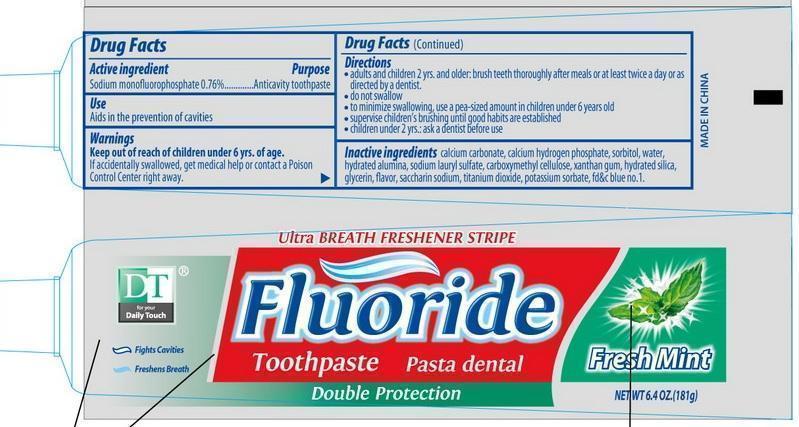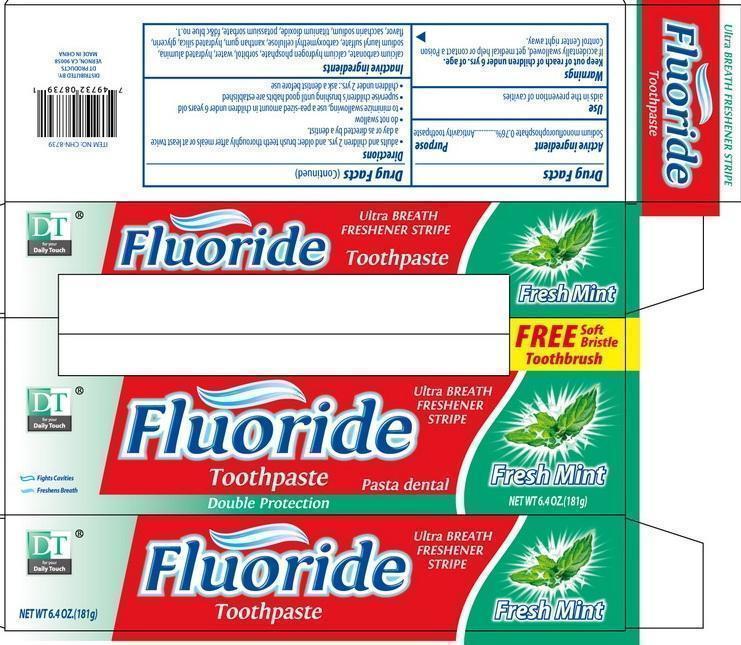 DRUG LABEL: DT Fluoride
NDC: 50523-739 | Form: PASTE, DENTIFRICE
Manufacturer: Volume Distributors, Inc.
Category: otc | Type: HUMAN OTC DRUG LABEL
Date: 20180216

ACTIVE INGREDIENTS: SODIUM MONOFLUOROPHOSPHATE 0.1 g/100 g
INACTIVE INGREDIENTS: CALCIUM CARBONATE; ANHYDROUS DIBASIC CALCIUM PHOSPHATE; SORBITOL; WATER; SODIUM LAURYL SULFATE; CARBOXYMETHYLCELLULOSE; XANTHAN GUM; HYDRATED SILICA; GLYCERIN; SACCHARIN SODIUM; TITANIUM DIOXIDE; POTASSIUM SORBATE; FD&C BLUE NO. 1

DT FLUORIDE TOOTHPASTE

Active Ingredient

Sodium Monofluorophosphate 0.76%

Purpose

Anticavity toothpaste

Uses

Aids in the prevention of cavities

WARNINGS

If accidentally swallowed, get medical help or contact a Poison Control Center right away.

Keep out of reach of children under 6 yrs of age.

Directions

adults and children 2 years. and older: brush teeth thoroughly after meals or at least twice a day or as directed by a dentist.

do not swallow

to minimize swallowing, use a pea-sized amount in children under 6 years old

supervise children's brushing until good habits are established

children under 2y ears: ask a dentist before use.

Inactive Ingredients

calcium carbonate, calcium hydrogen phosphate, sorbitol, water, hydrated alumina, sodium laryl sulfate, carboxymethylcellulose, xanthan gum, hydrated silica, glycerin, flavor, saccharin sodium, titanium dioxide, potassium sorbate FDandC blue no.1

Distributed by:

DT Products
Vernon, CA 90058

Made in China

PACKAGE LABEL

DT Fluoride Toothpaste

Ultra Breath Freshener Stripe

Net Wt 6.4oz (181g)

Fresh Mint